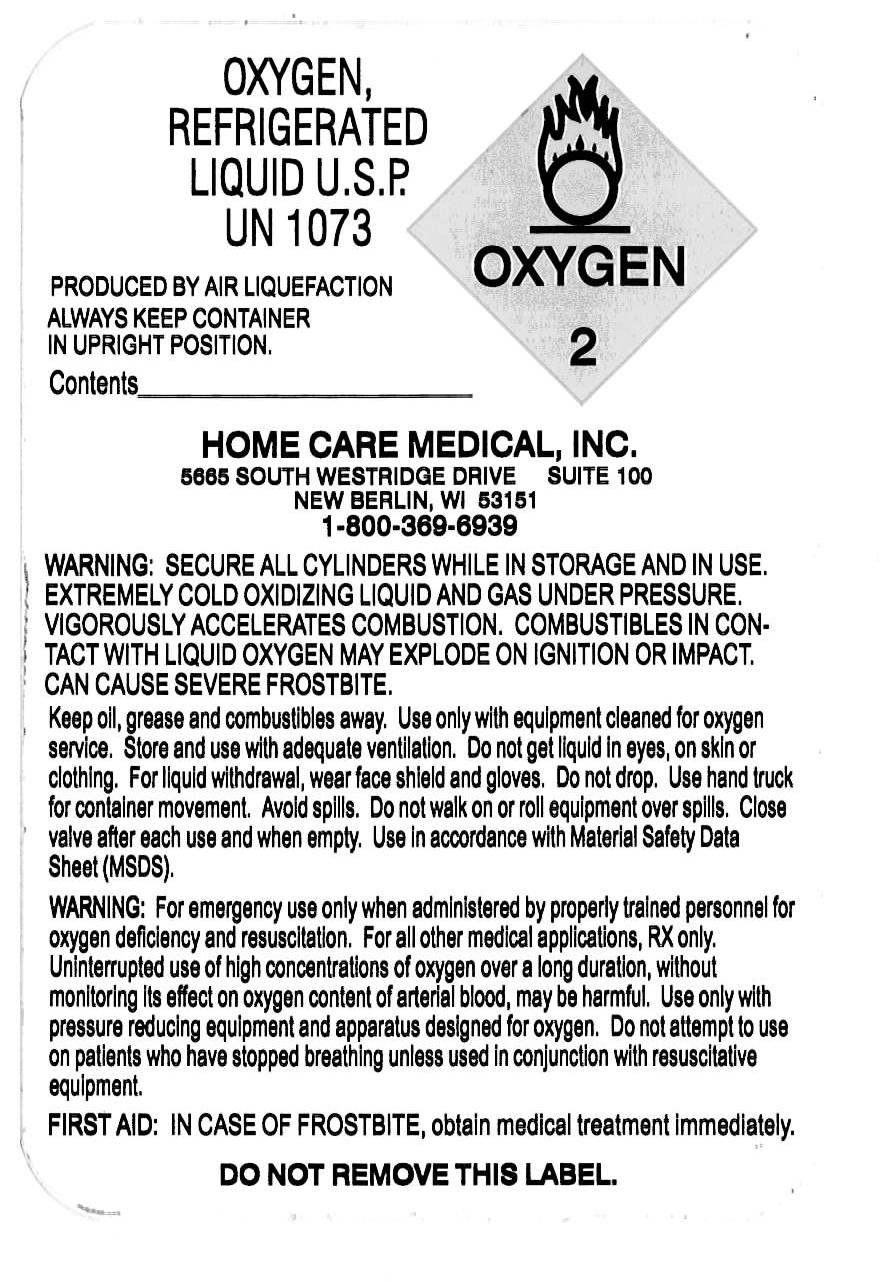 DRUG LABEL: Oxygen
NDC: 58120-001 | Form: GAS
Manufacturer: Home Care Medical, Inc
Category: prescription | Type: HUMAN PRESCRIPTION DRUG LABEL
Date: 20091204

ACTIVE INGREDIENTS: Oxygen 990 mL/1 L

Oxygen Label

PACKAGE LABEL

Enter section text here

OXYGEN REFRIGERATED LIQUID U.S.P. UN 1703

PRODUCED BY AIR LIQUEFACTION ALWAYS KEEP CONTAINER IN UPRIGHT POSITION.

Contents -------------------------

HOME CARE MEDICAL, INC.

5665 South Westridge Drive Suite 100

New Berlin, WI 53151

1-800-369-6939

WARNING: SECURE ALL CYLINDERS WHILE IN STORAGE AND IN USE. EXTREMELY COLD OXIDIZING LIQUID AND GAS UNDER PRESSURE. VIGOROUSLY ACCELERATES COMBUSTION. COMBUSTIBLES IN CONTACT WITH LIQUID OXYGEN MAY EXPLODE ON IGNITION OR IMPACT. CAN CAUSE SEVERE FROSTBITE.

Keep oil, grease and combustibles away. use only with equipment cleaned for oxygen service. Store and use with adequate ventilation. Do not get liquid in eyes, on skin or clothing. For liquid withdrawal, wear face shield and gloves. do not drop. Use hand truck for container movement. Avoid spills. Do not walk on or roll equipment over spills. Close valve after each use and when empty. Use in accordance with Material Safety Data Sheet (MSDS).

WARNING: For emergency use only when administered by properly trained personnel for oxygen deficiency and resuscitation. For all other medical applications, RX only. Uninterrupted use of high concentrations of oxygen over a long duration, without monitoring its effect on oxygen content of arterial blood, may be harmful. Use only with pressure reducing equipment and apparatus designed for oxygen. Do not attempt to use on patients who have stopped breathing unless used in conjunction with resuscitative equipment.

FIRST AID: IN CASE OF FROSTBITE, obtain medical treatment immediately.

DO NOT REMOVE THIS LABEL